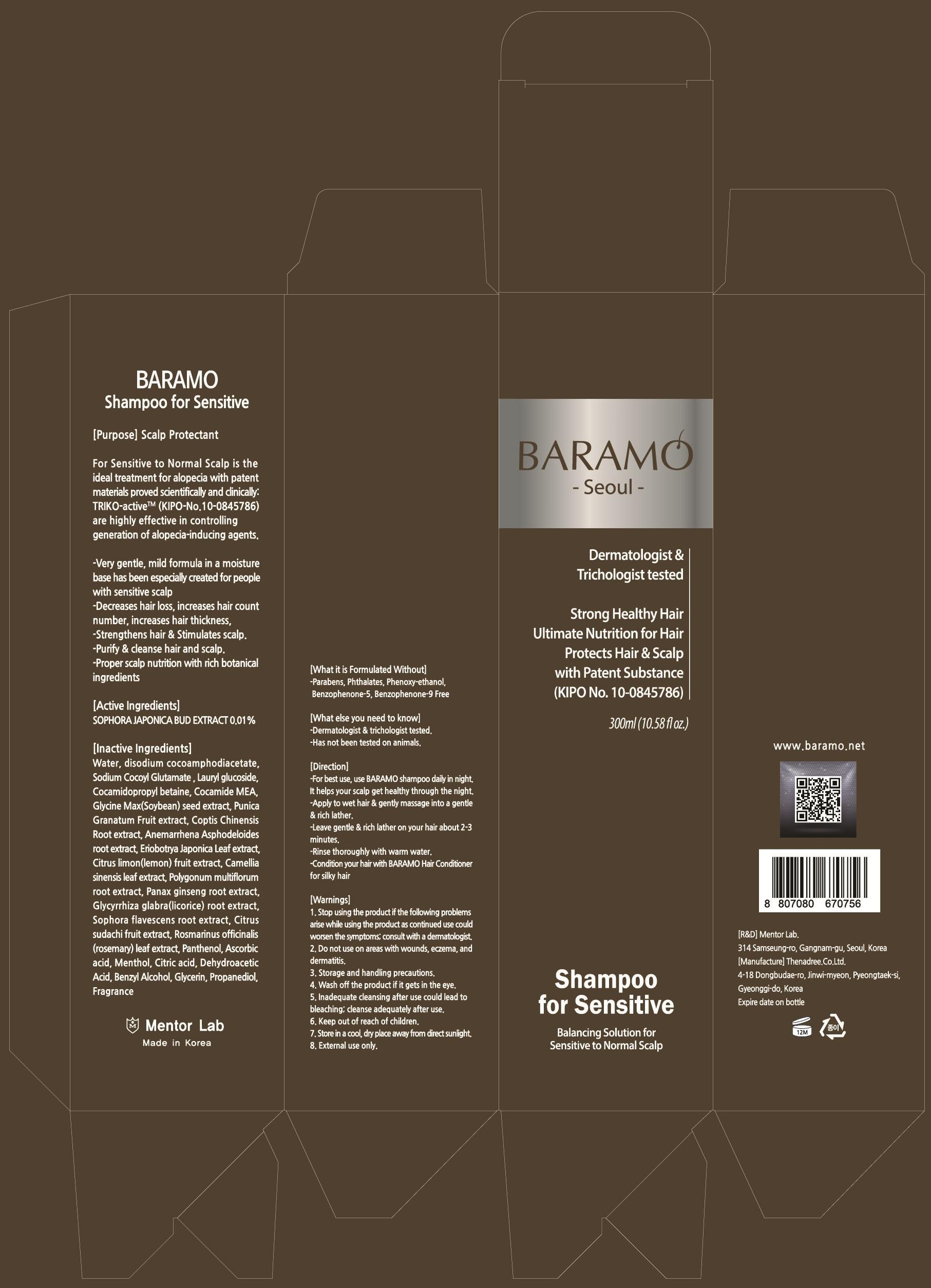 DRUG LABEL: BARAMO
NDC: 69961-010 | Form: SHAMPOO
Manufacturer: Mentor Lab
Category: otc | Type: HUMAN OTC DRUG LABEL
Date: 20150806

ACTIVE INGREDIENTS: STYPHNOLOBIUM JAPONICUM FLOWER BUD 0.3 mg/300 mL
INACTIVE INGREDIENTS: Water; Disodium cocoamphodiacetate

ACTIVE INGREDIENT

Active Ingredients: SOPHORA JAPONICA BUD EXTRACT 0.01%

INACTIVE INGREDIENT

Inactive Ingredients: Water, Disodium cocoamphodiacetate, Sodium Cocoyl Glutamate, Lauryl glucoside, Cocamidopropyl betaine, Cocamide MEA, Glycine Max(Soybean) seed extract, Punica Granatum Fruit extract, Coptis Chinensis Root extract, Anemarrhena Asphodeloides root extract, Eriobotrya Japonica Leaf extract, Citrus limon(lemon) fruit extract, Camellia sinensis leaf extract, Polygonum multiflorum root extract, Panax ginseng root extract, Glycyrrhiza glabra(licorice) root extract, Sophora flavescens root extract, Citrus sudachi fruit extract, Rosmarinus officinalis(rosemary) leaf extract, Panthenol, Ascorbic acid, Menthol, Citric acid, Dehydroacetic Acid, Benzyl Alcohol, Glycerin, Propanediol, Fragrance

PURPOSE

Propose: Scalp Protectant

WARNINGS

Warnings: 1. Stop using the product if the following problems arise while using the product as continued use could worsen the symptoms; consult with a dermatologist. 2. Do not use on areas with wounds, eczema, and dermatitis. 3. Storage and handling precautions. 4. Wash off the product if it gets in the eye. 5. Inadequate cleansing after use could lead to bleaching; cleanse adequately after use. 6. Keep out of reach of children. 7. Store in a cool, dry place away from direct sunlight. 8. External use only.

KEEP OUT OF REACH OF CHILDREN

Direction

-For best use, use BARAMO shampoo daily in night. It helps your scalp get healthy through the night. -Apply to wet hair & gently massage into a gentle & rich lather.

-Leave gentle & rich lather on your hair about 2-3 minutes.

-Rinse thoroughly with warm water.

-Condition your hair with BARAMO Hair Conditioner for silky hair

Direction

-For best use, use BARAMO shampoo daily in night. It helps your scalp get healthy through the night. -Apply to wet hair & gently massage into a gentle & rich lather.

-Leave gentle & rich lather on your hair about 2-3 minutes.

-Rinse thoroughly with warm water.

-Condition your hair with BARAMO Hair Conditioner for silky hair